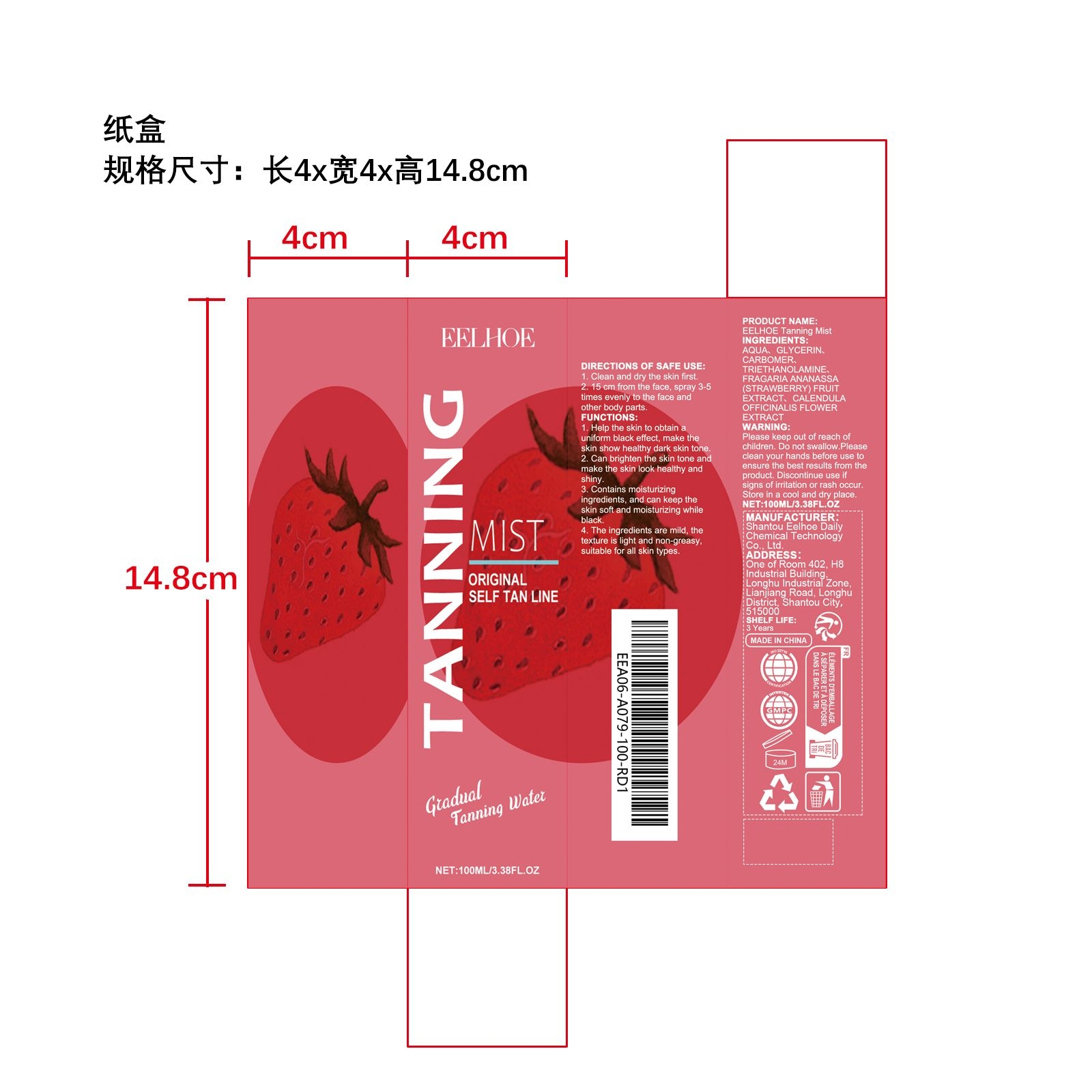 DRUG LABEL: EELHOE Tanning Mist
NDC: 85064-006 | Form: LIQUID
Manufacturer: Shantou Eelhoe Daily Chemical Technology Co., Ltd.
Category: otc | Type: HUMAN OTC DRUG LABEL
Date: 20251127

ACTIVE INGREDIENTS: FRAGARIA ANANASSA (STRAWBERRY) FRUIT 0.02 mg/100 mg; CALENDULA OFFICINALIS FLOWER 0.02 mg/100 mg
INACTIVE INGREDIENTS: TRIETHANOLAMINE 0.2 mg/100 mg; AQUA 91.56 mg/100 mg; GLYCERIN 8 mg/100 mg; CARBOMER 0.2 mg/100 mg

ACTIVE INGREDIENT

CALENDULA OFFICINALIS FLOWER、FRAGARIA ANANASSA (STRAWBERRY)

PURPOSE

1. Help the skin to obtain a uniform black effect, make the skin show healthy dark skin tone.

2. Can brighten the skin tone and make the skin look healthy and shiny.

3. Contains moisturizing ingredients, and can keep the skin soft and moisturizing while black.

4. The ingredients are mild, the texture is light and non -greasy, suitable for all skin types.

WHEN USING

1. Clean and dry the skin first

2. 15 cm from the face, spray 3-5 times evenly to the face and other body parts

DO NOT USE

Discontinue use if signs of irritation or rash occur.

STOP USE

Discontinue use if signs of irritation or rash occur.

KEEP OUT OF REACH OF CHILDREN

Please keep out of reach of children. Do not swallow.

WARNINGS

Please keep out of reach of children. Do not swallow.Please clean your hands before use to ensure the best results from the product. Discontinue use if signs of irritation or rash occur. Store in a cool and dry place.

STORAGE AND HANDLING

Store in a cool and dry place.

INACTIVE INGREDIENT

AQUA
GLYCERIN
CARBOMER
TRIETHANOLAMINE